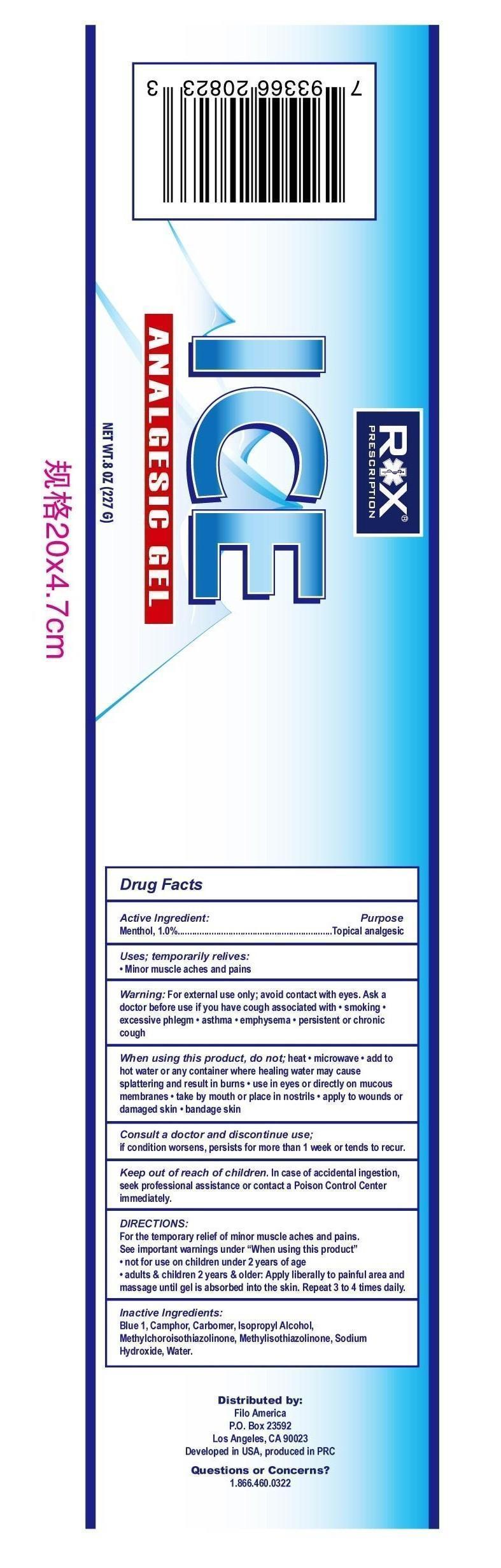 DRUG LABEL: Ice ANALGESIC
NDC: 50438-501 | Form: GEL
Manufacturer: Filo America
Category: otc | Type: HUMAN OTC DRUG LABEL
Date: 20150505

ACTIVE INGREDIENTS: MENTHOL 1.0 g/100 g
INACTIVE INGREDIENTS: CAMPHOR (NATURAL); ALCOHOL; FD&C BLUE NO. 1; ISOPROPYL ALCOHOL; METHYLCHLOROISOTHIAZOLINONE; SODIUM HYDROXIDE; WATER

ICE ANALGESIC GEL

Active Ingredient

Menthol 1.0%

Purpose

Topical Analgesic

Uses

Temporary relief:

minor muscles aches and pains

Warnings

For external use only. Avoid contact with eyes.

Ask a doctor before use if you have cough associated with

- smoking
- excessive phlegm
- asthma
- emphysema
- persistent or chronic cough

When using this product do not

- heat
- microwave
- add to hot water or any container where healing water may cause splattering and result in burns
- use in eyes or directly on mucous membranes
- take by mouth or place in nostrils
- apply to wounds or damaged skin
- bandage skin

Consult a doctor and discontinue use

if condition worsens, persist for more than 1 week or tends to recur

Keep out of reach of children.

In case of accidental ingestion, seek professional assistance or contact a Poison Control Center immediately.

Directions

For the temporary relief of minor muscle aches and pains

see important warnings under "When using this product"

- not for use on children under 2 years of age
- adults and children 2 years of age and older: apply to painful area and massage until gel is absorbed into the skin, repeat 3 to 4 times daily

Inactive Ingredients

blue 1, camphor, carbomer, isopropyl alcohol, methylchoroisothiazolinone, methuylisothiazoline, sodium hydroxide, water

PACKAGE LABEL

ICE Analgesic Gel

Net wt 8oz (227g)

DISTRIBUTED BY:

Filo America

P.O. Box 23592

Los Angeles, CA 90023

Developed in USA, products in PRC

questions or concerns?

1.866.460.0322